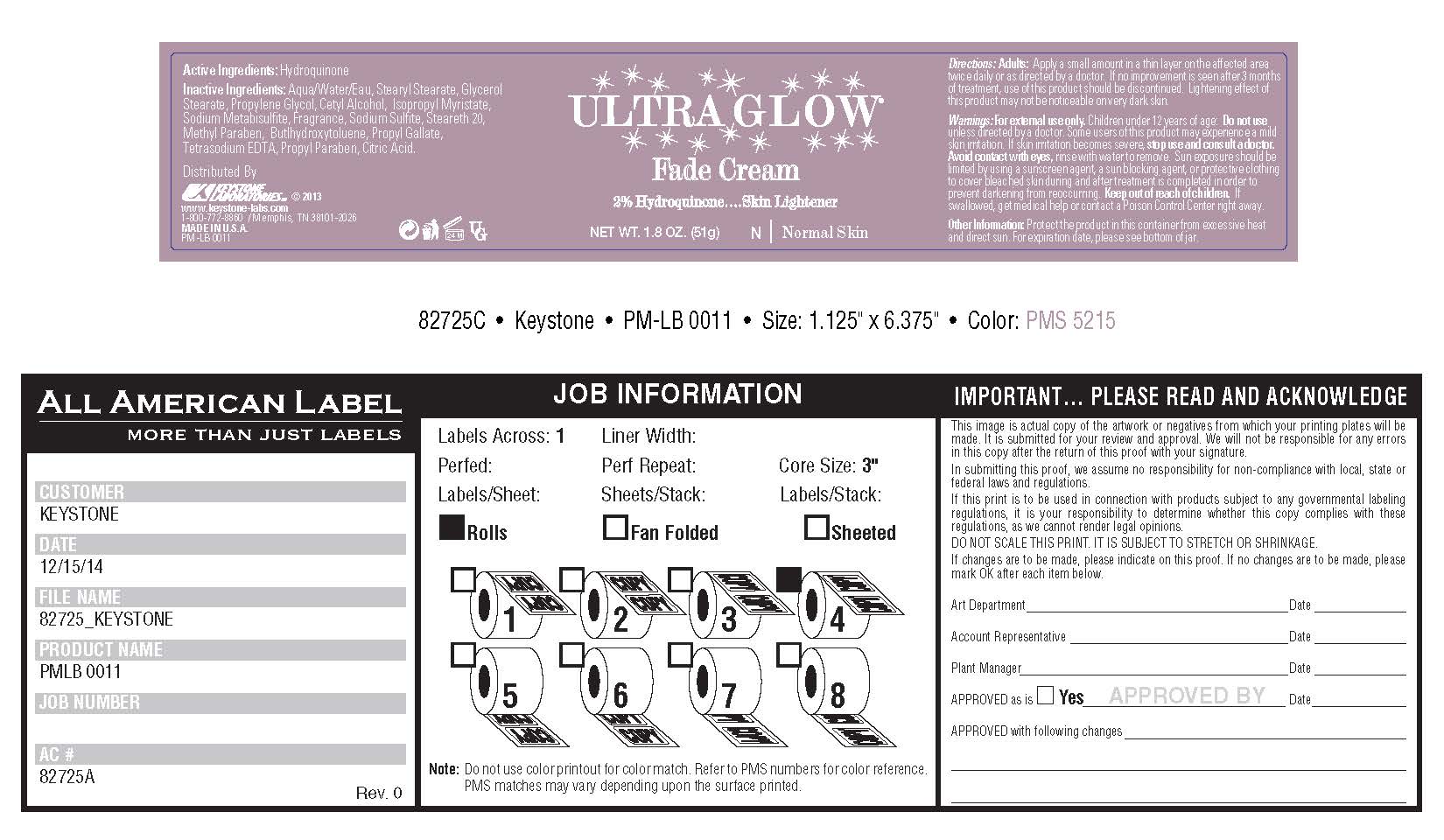 DRUG LABEL: Ultra Glow Fade
NDC: 58318-003 | Form: CREAM
Manufacturer: Keystone Laboratories
Category: otc | Type: HUMAN OTC DRUG LABEL
Date: 20180110

ACTIVE INGREDIENTS: HYDROQUINONE 1 g/51 g
INACTIVE INGREDIENTS: WATER; GLYCERYL MONOSTEARATE; SODIUM LAURYL SULFATE; PROPYLENE GLYCOL; ISOPROPYL MYRISTATE; CETYL ALCOHOL; SODIUM METABISULFITE; STEARYL STEARATE; STEARETH-20; METHYLPARABEN; PROPYLPARABEN; BUTYLATED HYDROXYTOLUENE; PROPYL GALLATE; SODIUM SULFITE; EDETATE DISODIUM; CITRIC ACID MONOHYDRATE; METHYL ALCOHOL

ACTIVE INGREDIENT

2% Hydroquinone ..... Skin Lightener

Keep out of reach of children. If swallowed, get medical help or contact a Poison Control Center right away.

PURPOSE

Skin lightener

INDICATIONS AND USAGE

Ultra Glow Fade Cream

2% Hydroquinone ...... Skin Lightener

Warnings:

For external use only. Children under 12 years of age: Do not use unless directed by a doctor. Some users of this product may experience a mild skin irritation. If skin irritation becomes severe, stop use and consult a doctor. Avoid contact with eyes, rinse with water to remove. Sun exposure should be limited by using a sunscreen agent, a sun blocking agent, or protective clothing to cover bleached skin during and after treatment is completed in order to prevent darkening from reoccurring. Keep out of reach of children. If swallowed, get medical help or contact a Poison Control Center right away.

Directions:

Adults: Apply a small amount in a thin layer on the affected area twice daily or as directed by a doctor. If no improvement is seen after 3 months of treatment, use of this product should be discontinued. Lightening effect of this product may not be noticeable on very dark skin.

Other Information: Protect the product in this container from excessive heat and direct sun. For expiration date, please see bottom of jar.

Distributed by

KEYSTONE LABORATORIES © 2013

www.keystone-labs.com

1-800-772-8860 / Memphis, TN 38101-2026

MADE IN U.S.A.

PM-LB 0011

Inactive Ingredients:

Aqua/Water/Eau, Stearyl Stearate, Glycerol Stearate, Propylene Glycol Alcohol, Isopropyl Myristate, Sodium Metabisulfite, Fragrance, Sodium Sulfite, Steareth 20, Methyl Paraben, Buthydroxytoluene, Propyl Gallate, Tetrasodium EDTA, Propyl Paraben, Citric Acid